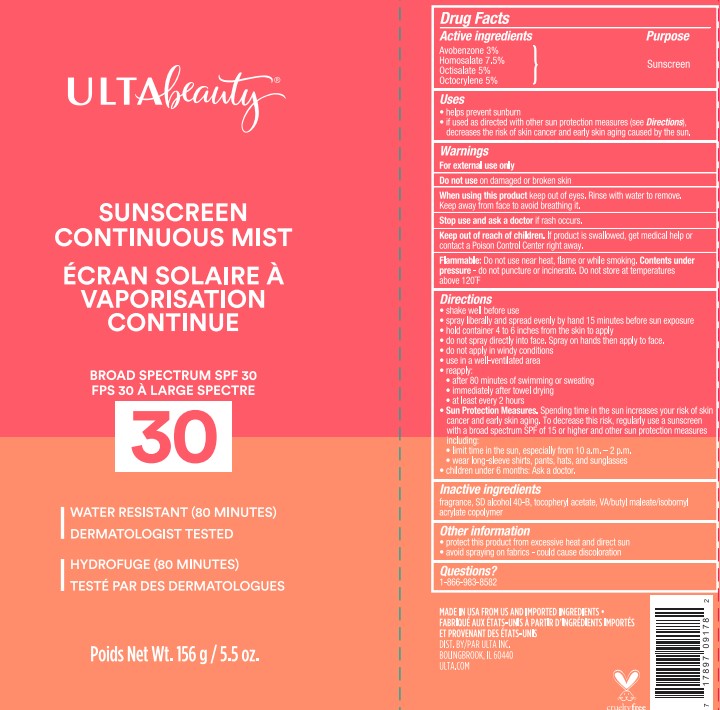 DRUG LABEL: Ulta Beauty
NDC: 13630-0176 | Form: SPRAY
Manufacturer: Prime Packaging, Inc.
Category: otc | Type: HUMAN OTC DRUG LABEL
Date: 20220302

ACTIVE INGREDIENTS: AVOBENZONE 3 g/100 g; HOMOSALATE 7.5 g/100 g; OCTISALATE 5 g/100 g; OCTOCRYLENE 5 g/100 g
INACTIVE INGREDIENTS: ALCOHOL; ALPHA-TOCOPHEROL ACETATE; COCONUT OIL

Ulta Beauty Sunscreen Continuous Mist Broad Spectrum SPF 30

Active ingredients

Avobenzone 3%

Homosalate 7.5%

Octisalate 5%

Octocrylene 5%

Purpose

Sunscreen

Uses

helps prevent sunburn

if used as directed with other sun protection measures (see Directions, decreases the risk of skin cancer and early skin aging caused by the sun.

Warnings

For external use only

Do not use

on damaged or broken skin

When using this product

keep out of eyes. Rinse with water to remove. Keep away from face to avoid breathing it.

Stop use and ask a doctor

if rash occurs.

Keep out of reach of children.

If product is swallowed, get medical help or contact a Poision Control Center right away.

Flammable:

Do not use near heat, flame or while smoking.

Contents under pressure - do not puncture or incinerate.

Do not store at temperatures above 120°F

Directions

shake well before use

spray liberally and spread evenly by hand 15 minutes before sun exposure

hold container 4 to 6 inches from the skin to apply

do not spray directly into face. Spray on hands then apply to face.

do not apply in windy conditions

use in a well-ventilated area

reapply:

after 80 minutes of swimming or sweating

immediately after towel drying

at least every 2 hours

Sun Protection Measures. Spending time in the sun increases your risk of skin cancer and early skin aging. To decrease this risk, regularly use a sunscreen with a broad spectrum SPF of 15 or higher and other sun protection measures including:

limit time in the sun, especially from 10 a.m. - 2 p.m.

wear long-sleeve shirts, pants, hats, and sunglasses

children under 6 months: Ask a doctor.

Inactive ingredients

Fragrance, SD Alcohol 40-B, Tocopheryl Acetate, VA/Butyl Maleate/Isobromyl Acrylate Copolymer

Other information

protect this product from excessive heat and direct sun

avoid spraying on fabrics - could cause discoloration

Questions or comments?

Call 1-866-983-8582